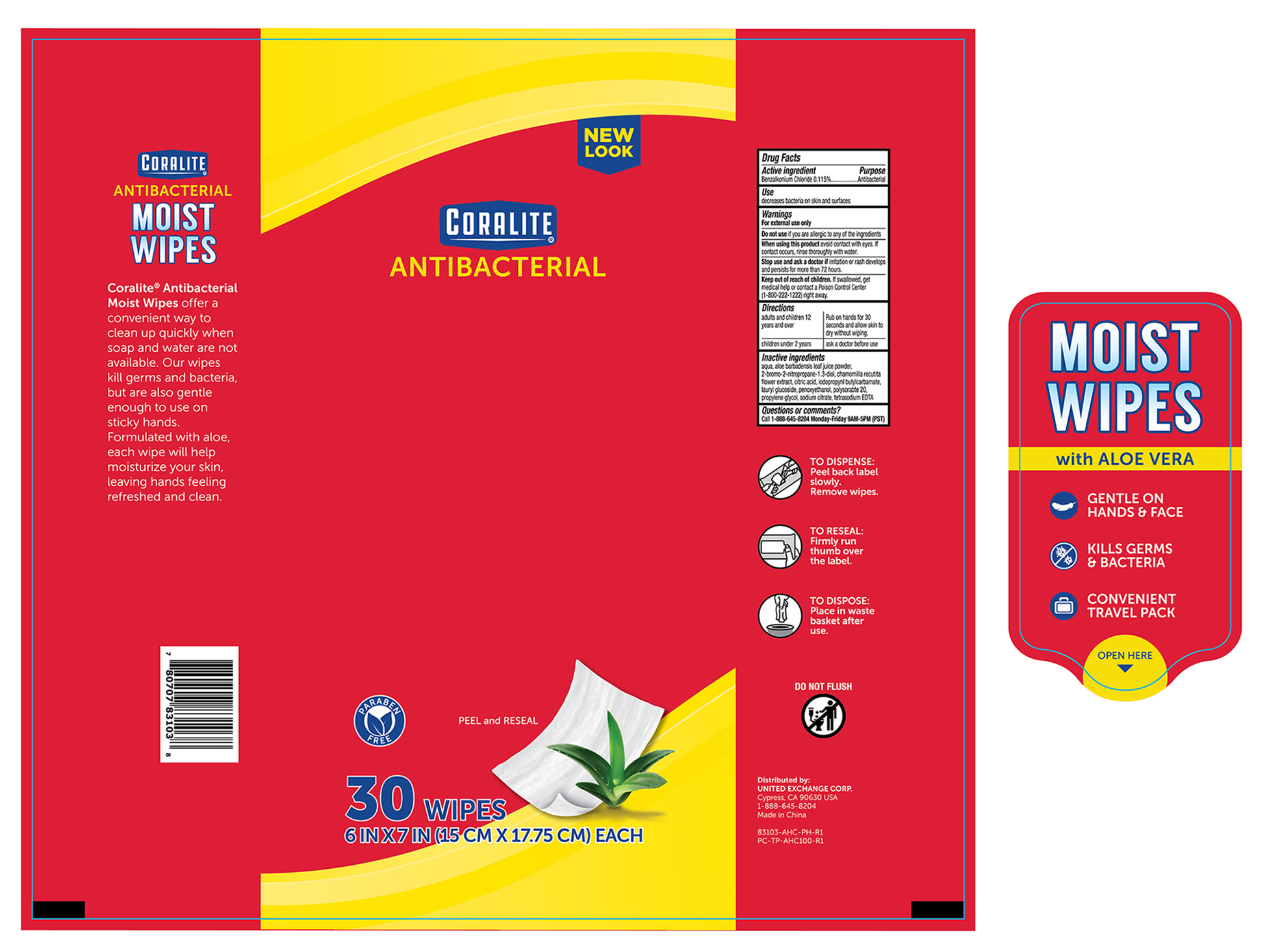 DRUG LABEL: Coralite Antibacterial Moist
NDC: 65923-831 | Form: SOLUTION
Manufacturer: United Exchange Corp.
Category: otc | Type: HUMAN OTC DRUG LABEL
Date: 20251031

ACTIVE INGREDIENTS: BENZALKONIUM CHLORIDE 0.115 g/1 1
INACTIVE INGREDIENTS: ALOE VERA LEAF; BRONOPOL; CITRIC ACID ACETATE; LAURYL GLUCOSIDE; PHENOXYETHANOL; POLYSORBATE 20; PROPYLENE GLYCOL; SODIUM CITRATE; EDETATE SODIUM; WATER; MATRICARIA CHAMOMILLA ROOT

Coralite Antibacterial Moisturizing Pouch Wipe, 30ct 83103

Drug Facts

Active Ingredient Purpose

Benzalkonium Chloride 0.115%............................................................ Antibacterial

Uses

- Decreases bacteria on skin and surfaces

Warnings

For external use only

When using this product avoid contact with the eyes, if contact occurs rinse thoroughly with water.

Stop use and ask a doctor if

- Irritation or rash develops and persists for more than 72 hours.

Keep out of reach of children. If swallowed, get medical help or contact a Poision Control Center right away.

Directions

adults and children 12 years and over | Rub on hands for 30 seconds and allow skin to dry without wiping
children under 2 years | ask a doctor before use

Inactive ingredients

aqua, aloe barbadensis leaf juice powder, 2-Bromo-2-Nitropropane-1,3-Diol, Chamomilla Recutita Flower Extract, Citric Acid, Iodopropynl butylcarbamate, Lauryl Glucoside, Phenoxyethanol, Polysorbate 20, Propylene Glycol, Sodium Citrate, Terasodium EDTA

DOSAGE AND ADMINISTRATION

Distributed by:

UNITED EXCHANGE CORP.

17211 Valley View Ave.

Cerritos, CA 90703

MADE IN CHINA